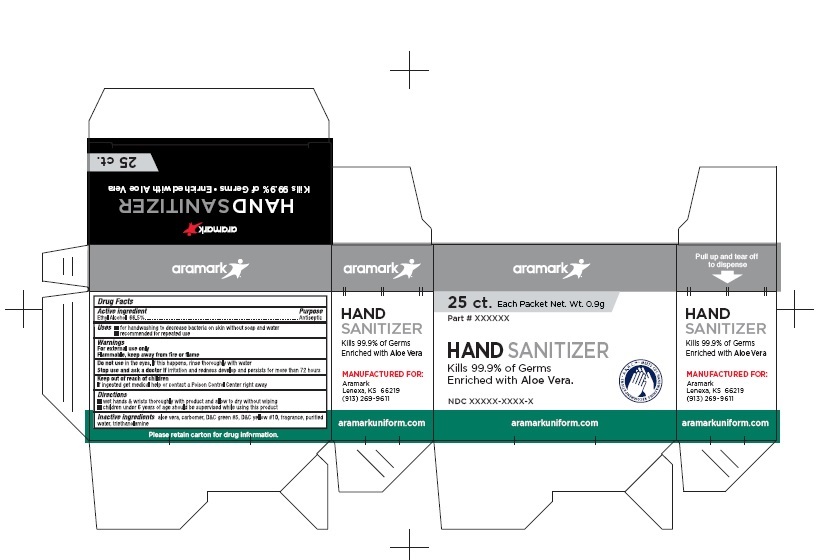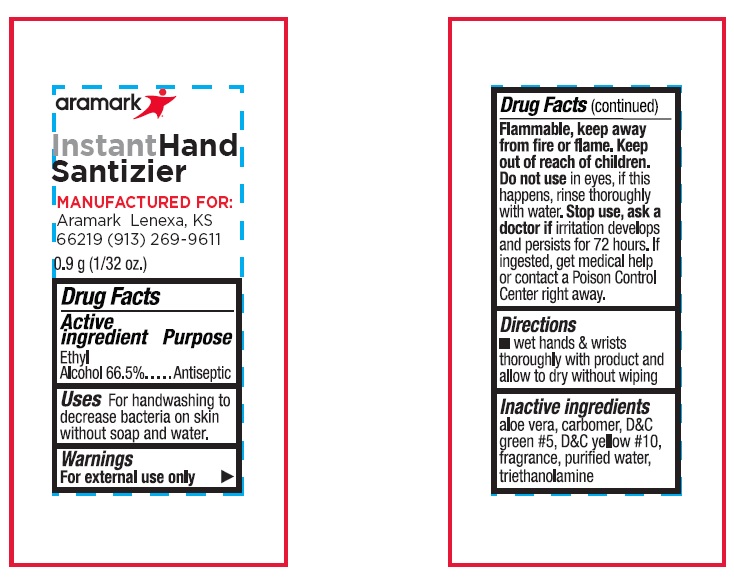 DRUG LABEL: Aramark Hand Sanitizer
NDC: 81238-1112 | Form: GEL
Manufacturer: Western First Aid Safety DBA Aramark
Category: otc | Type: HUMAN OTC DRUG LABEL
Date: 20210520

ACTIVE INGREDIENTS: ALCOHOL 66.5 mL/100 mL
INACTIVE INGREDIENTS: ALOE; CARBOMER HOMOPOLYMER, UNSPECIFIED TYPE; D&C GREEN NO. 5; D&C YELLOW NO. 10; WATER; TROLAMINE

aramark Hand Sanitizer

Active Ingredient

Ethyl Alcohol 66.5%

Purpose

Antibacterial

Uses

■ for hand washing to decrease bacteria on skin without soap and water

■ recommended for repeated use

Warnings

For external use only.

Flammable., keep away from fire or flame.

Do not use in eyes.

If this happens, rinse eyes thoroughly with water.

Stop use and ask a doctor if

irritation and redness develop and persists for more than 72 hours

Keep out of reach of children.

If ingested get medical help or contact a Poison Control Center right away.

Directions

■ wet hands and wrists thoroughly with product and allow to dry without wiping

■ children under 6 years of age should be supervised while using this product

Inactive Ingredients

aloe vera, carbomer, D&C green #5, D&C yellow #10, fragrance, purified

water, triethanolamine

Package Labeling

aramark

25 ct. Each Packet Net. Wt. 0.9g

HAND SANITIZER

Kills 99.9% of Germs

Enriched with Aloe Vera

NDC 81238-1112-2

aramarkuniform.com

MANUFACTURED FOR:

Aramark

Lenexa, KS 66219

(913) 269-9611

Please retain carton for drug information.

res